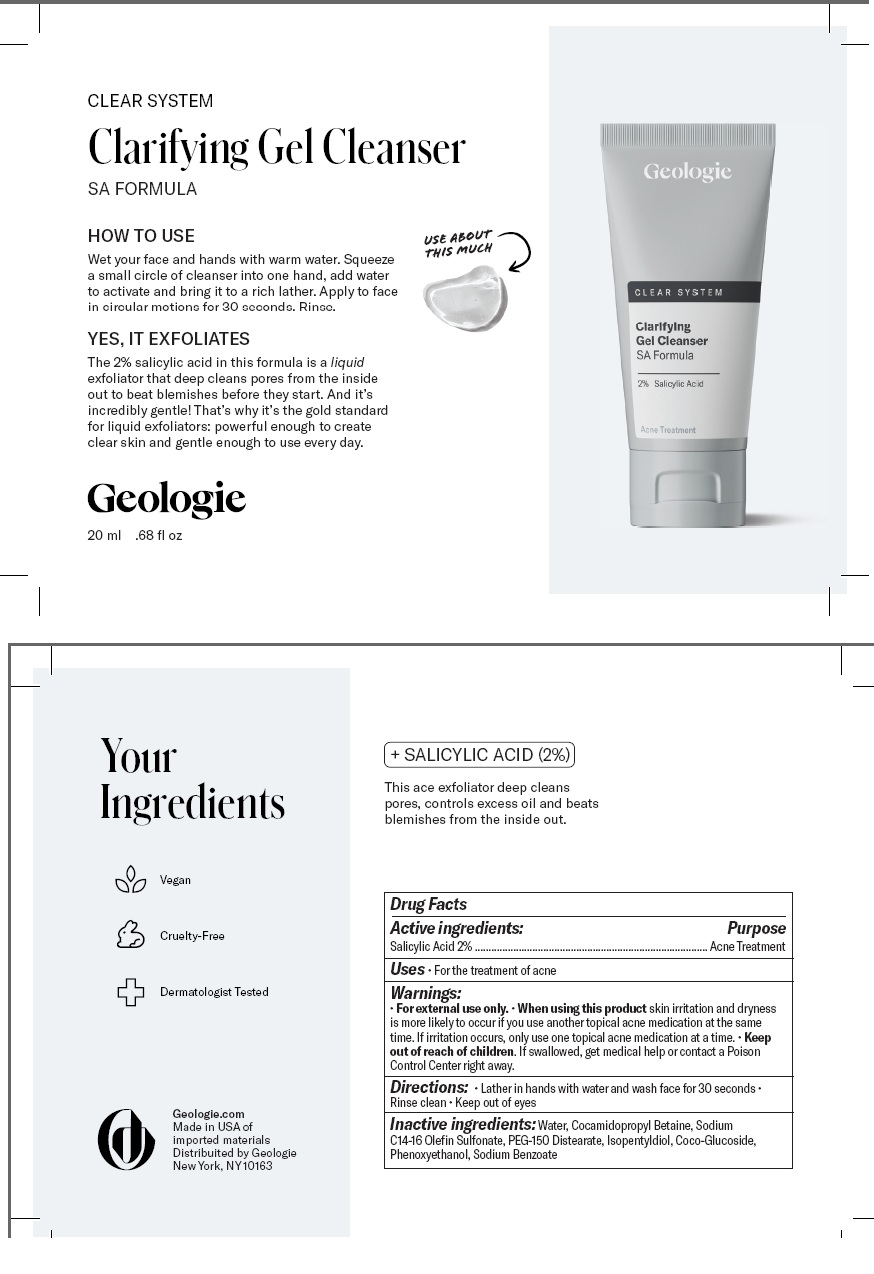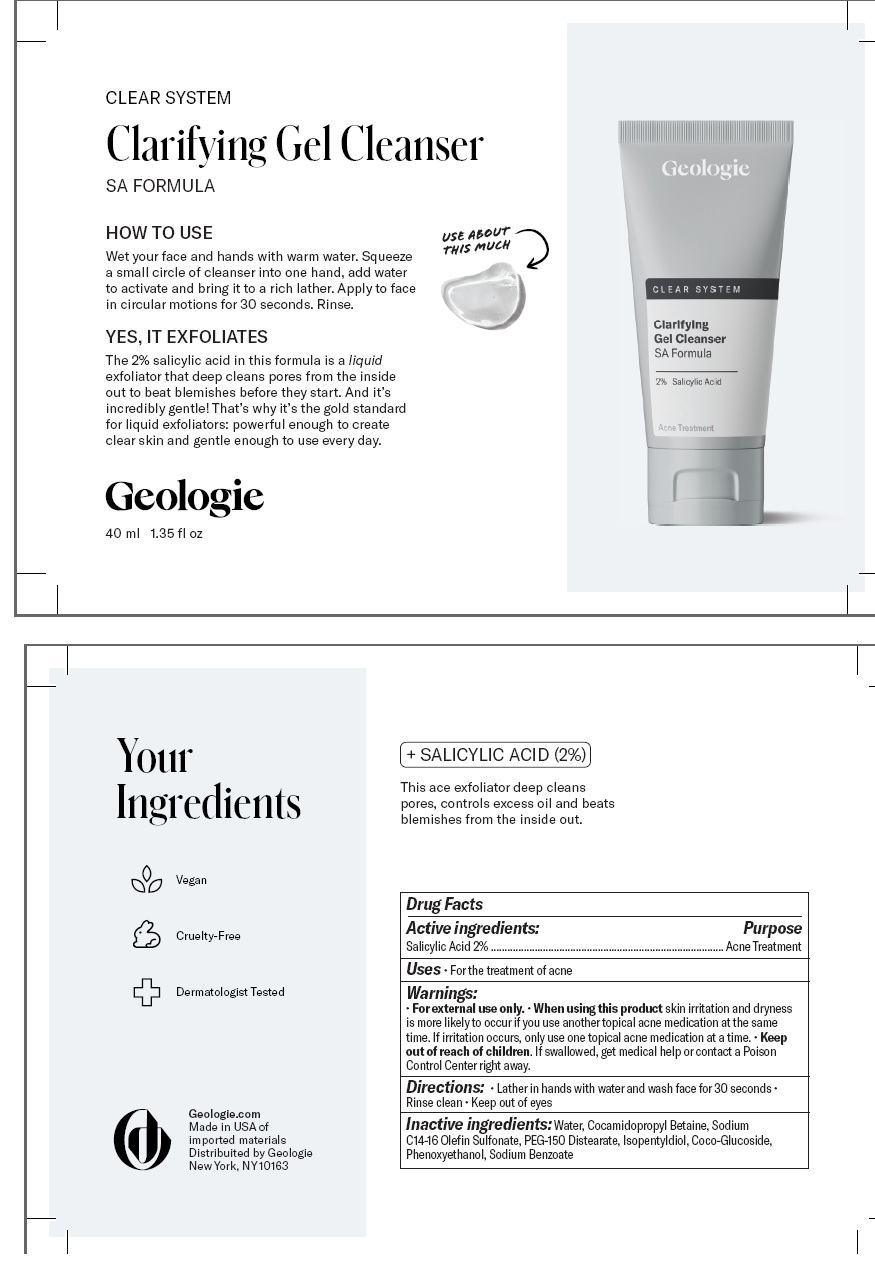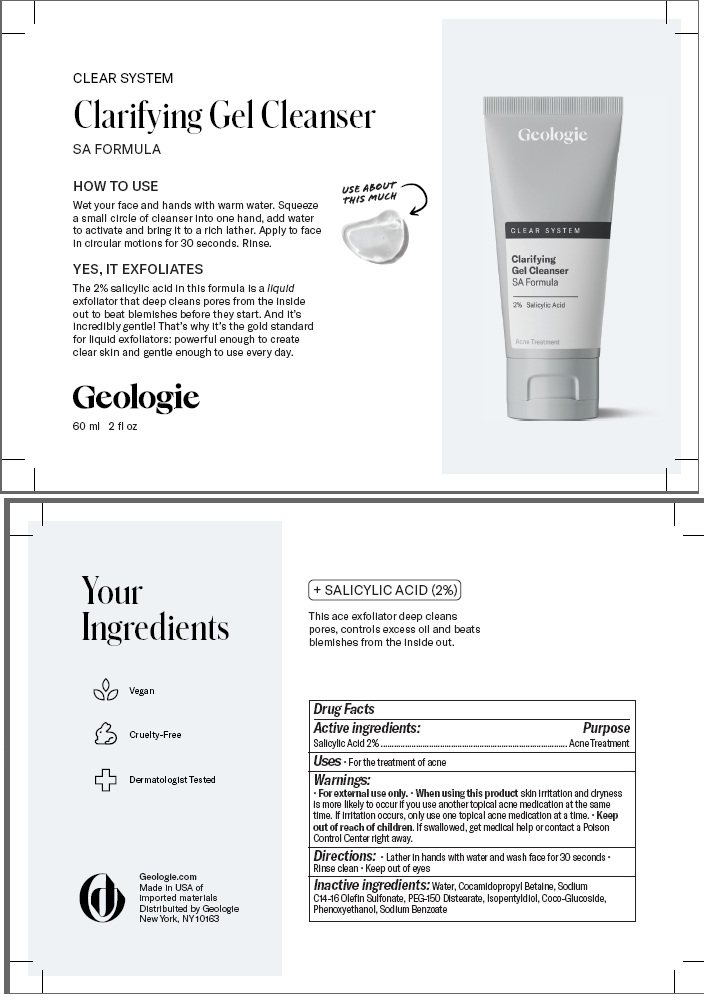 DRUG LABEL: Clear System Clarifying Gel Cleanser
NDC: 54111-189 | Form: GEL
Manufacturer: Bentley Laboratories, LLC
Category: otc | Type: HUMAN OTC DRUG LABEL
Date: 20241204

ACTIVE INGREDIENTS: SALICYLIC ACID 2.0 g/100 mL
INACTIVE INGREDIENTS: WATER; COCAMIDOPROPYL BETAINE; SODIUM C14-16 OLEFIN SULFONATE; PEG-150 DISTEARATE; ISOPENTYLDIOL; COCO-GLUCOSIDE; PHENOXYETHANOL; SODIUM BENZOATE

Geologie Clear System Clarifying Gel Cleanser SA Formula

DRUG FACTS

Active Ingredients: Salicylic Acid 2%

Purpose Acne Treatment

INDICATIONS AND USAGE

Uses • For the treatment of acne

Warnings:

• For external use only. When using this product skin irritation and dryness

is more likely to occur if you use another topical acne medication at the same

time. If irritation occurs, only use one topical acne medication at a time.

KEEP OUT OF REACH OF CHILDREN

• Keep out of the reach of children. If swallowed get medical help

or contact a Poison Control center right away.

DOSAGE AND ADMINISTRATION

Directions: • Lather in hands with water and wash face for 30 seconds

• Rinse clean • Keep out of eyes

Inactive ingredients: Water, Cocamidopropyl Betaine, Sodium
C14-16 Olefin Sulfonate, PEG-150 Distearate, Isopentyldiol, Coco-Glucoside,
Phenoxyethanol, Sodium Benzoate

Geologie Clear System Clarifying Gel Cleanser Labeling

CLEAR SYSTEM

Clarifying Gel Cleanser

Geologie

20 mL .68 fl oz

40 mL 1.35 fl oz

60 mL 2 fl ozz

Geologie.com
Made in USA of
Imported Materials
Distributed by Geologie
New York, NY 10025

20 mL Tube

40 mL Tube

60 mL Tube

res